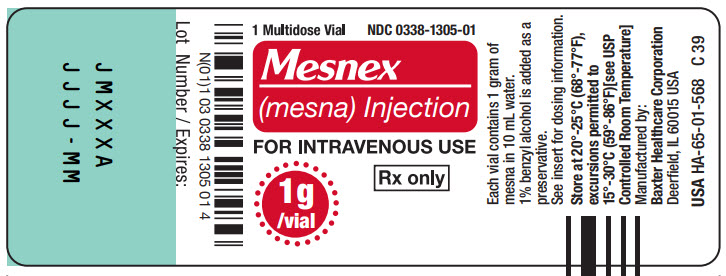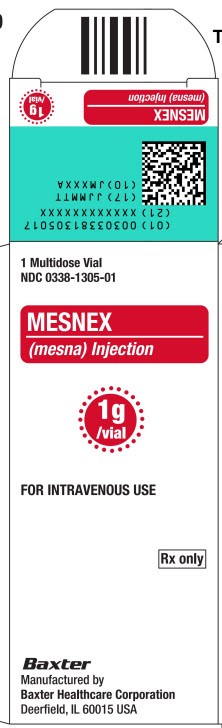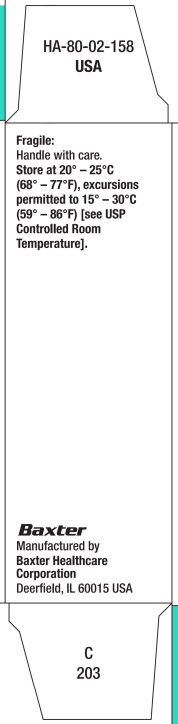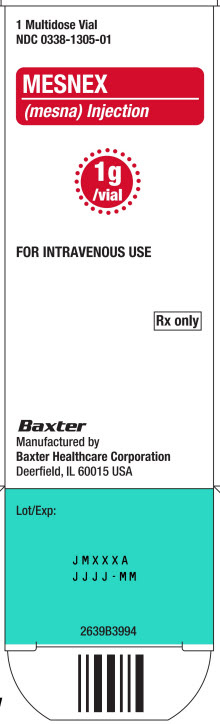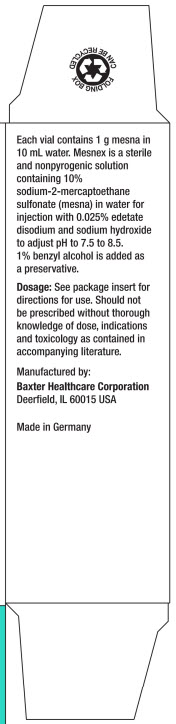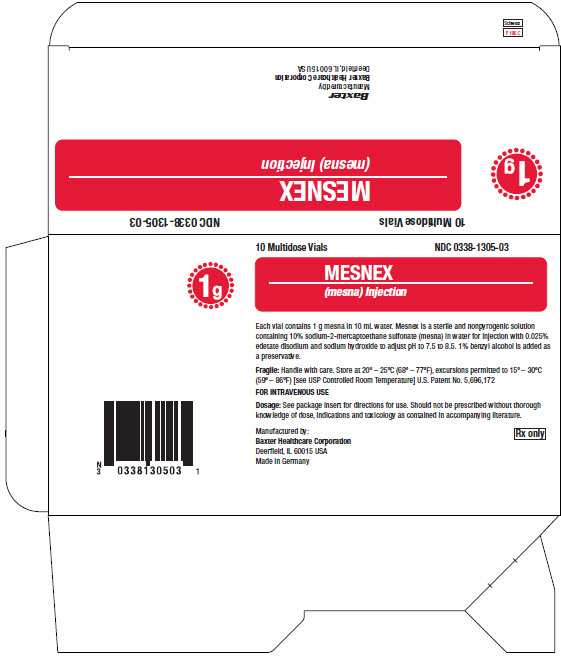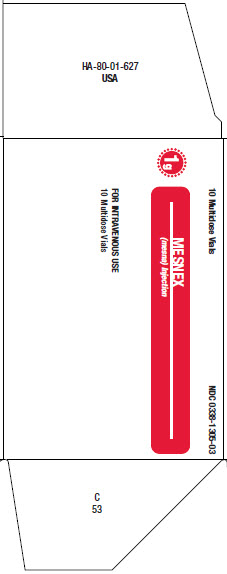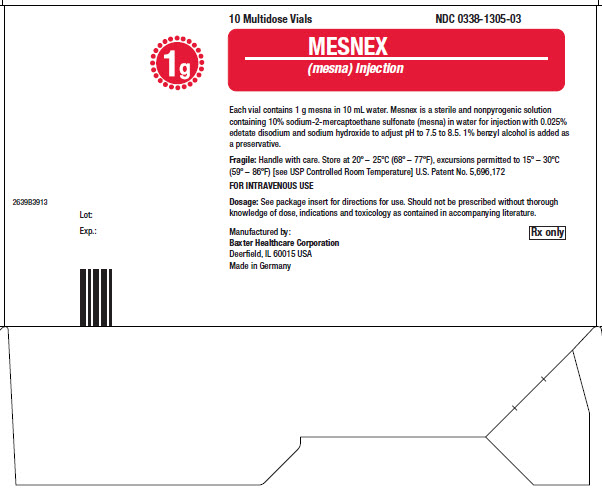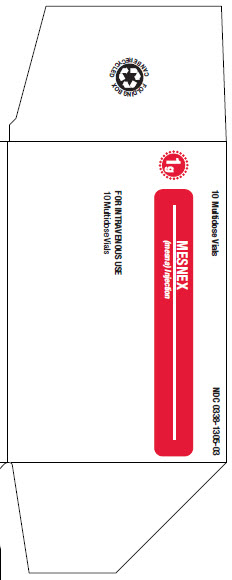 DRUG LABEL: MESNEX
NDC: 83703-559 | Form: INJECTION, SOLUTION
Manufacturer: Bamboo US Bidco LCC
Category: prescription | Type: HUMAN PRESCRIPTION DRUG LABEL
Date: 20251210

ACTIVE INGREDIENTS: MESNA 100 mg/1 mL
INACTIVE INGREDIENTS: EDETATE DISODIUM 0.25 mg/1 mL; SODIUM HYDROXIDE; BENZYL ALCOHOL 1.04 mg/1 mL

HIGHLIGHTS OF PRESCRIBING INFORMATION

These highlights do not include all the information needed to use MESNEX safely and effectively. See full prescribing information for MESNEX.
MESNEX (mesna) tablets, for oral use
MESNEX (mesna) injection, for intravenous use
Initial U.S. Approval: 1988

RECENT MAJOR CHANGES

Warnings and Precautions, Benzyl Alcohol Toxicity (5.3) 12/2018

1 INDICATIONS AND USAGE

MESNEX is a cytoprotective agent indicated as a prophylactic agent in reducing the incidence of ifosfamide-induced hemorrhagic cystitis. (1)

Limitation of Use:

MESNEX is not indicated to reduce the risk of hematuria due to other pathological conditions such as thrombocytopenia. (1)

2 DOSAGE AND ADMINISTRATION

MESNEX may be given on a fractionated dosing schedule of three bolus intravenous injections or a single bolus injection followed by two oral administrations of MESNEX tablets as outlined below. The dosing schedule should be repeated on each day that ifosfamide is administered. When the dosage of ifosfamide is adjusted, the ratio of MESNEX to ifosfamide should be maintained. (2)

Intravenous Dosing Schedule:
 | 0 Hours | 4 Hours | 8 Hours
Ifosfamide | 1.2 g/m^2 | -- | --
MESNEX injection | 240 mg/m^2 | 240 mg/m^2 | 240 mg/m^2

Intravenous and Oral Dosing Schedule:
 | 0 Hours | 2 Hours | 6 Hours
Ifosfamide | 1.2 g/m^2 | -- | --
MESNEX injection | 240 mg/m^2 | -- | --
MESNEX tablets | -- | 480 mg/m^2 | 480 mg/m^2

Maintain sufficient urinary output, as required for ifosfamide treatment, and monitor urine for the presence of hematuria. (2.3)

3 DOSAGE FORMS AND STRENGTHS

1. Injection: 1g (100 mg/mL) Multidose vials (3)
2. Tablets: 400 mg with functional score (3)

4 CONTRAINDICATIONS

1. Known hypersensitivity to mesna or to any of the excipients, including benzyl alcohol. (4)

5 WARNINGS AND PRECAUTIONS

1. Hypersensitivity reactions: Anaphylactic reactions have been reported. Less severe hypersensitivity reactions may also occur. Monitor patients. If a reaction occurs, discontinue MESNEX and provide supportive care. (5.1)
2. Dermatologic toxicity: Skin rash with eosinophilia and systemic symptoms, Stevens-Johnson syndrome, and toxic epidermal necrolysis have occurred. Skin rash, urticaria, and angioedema have also been seen. Monitor patients. If a reaction occurs, discontinue MESNEX and provide supportive care. (5.2)
3. Benzyl alcohol toxicity: Serious and fatal adverse reactions can occur in premature neonates and low-birth weight infants treated with benzyl alcohol-preserved drugs, including MESNEX injection. Avoid use in premature neonates and low-birth weight infants. (5.3)
4. Laboratory test alterations: False positive tests for urinary ketones and interference with enzymatic CPK activity tests have been seen. (5.4)

6 ADVERSE REACTIONS

The most common adverse reactions (> 10%) when MESNEX is given with ifosfamide are nausea, vomiting, constipation, leukopenia, fatigue, fever, anorexia, thrombocytopenia, anemia, granulocytopenia, diarrhea, asthenia, abdominal pain, headache, alopecia, and somnolence. (6.1)

To report SUSPECTED ADVERSE REACTIONS, contact Baxter Healthcare at 1-866-888-2472, or FDA at 1-800-FDA-1088 or www.fda.gov/medwatch

8 USE IN SPECIFIC POPULATIONS

1. Pregnancy: MESNEX in combination with ifosfamide can cause fetal harm. Advise patients of potential risk to a fetus. (8.1)
2. Lactation: Do not breastfeed. (8.2)
3. Females and Males of Reproductive Potential: Advise patients to use effective contraception. Verify pregnancy status prior to initiation of MESNEX in combination with ifosfamide. (8.3)
4. Pediatric use: In premature neonates and low-birth weight infants, avoid use of benzyl alcohol–containing solutions. (8.4)
5. Geriatric use: Dose selection should be cautious. (8.5)

FULL PRESCRIBING INFORMATION

1 INDICATIONS AND USAGE

MESNEX is indicated as a prophylactic agent in reducing the incidence of ifosfamide-induced hemorrhagic cystitis.

Limitation of Use:
MESNEX is not indicated to reduce the risk of hematuria due to other pathological conditions such as thrombocytopenia.

2 DOSAGE AND ADMINISTRATION

2.1 Intravenous Dosing

MESNEX may be given on a fractionated dosing schedule of three bolus intravenous injections as outlined below.

MESNEX injection is given as intravenous bolus injections in a dosage equal to 20% of the ifosfamide dosage weight by weight (w/w) at the time of ifosfamide administration and 4 and 8 hours after each dose of ifosfamide. The total daily dose of MESNEX is 60% of the ifosfamide dose. The recommended dosing schedule is outlined below in Table 1.

Table 1. Recommended Intravenous Dosing Schedule
 | 0 Hours | 4 Hours | 8 Hours
Ifosfamide | 1.2 g/m^2 | – | –
MESNEX injection [The dosing schedule should be repeated on each day that ifosfamide is administered. When the dosage of ifosfamide is increased or decreased, the ratio of MESNEX to ifosfamide should be maintained.] | 240 mg/m^2 | 240 mg/m^2 | 240 mg/m^2

2.2 Intravenous and Oral Dosing

MESNEX may be given on a fractionated dosing schedule of a single bolus injection followed by two oral administrations of MESNEX tablets as outlined below.

MESNEX injection is given as intravenous bolus injections in a dosage equal to 20% of the ifosfamide dosage (w/w) at the time of ifosfamide administration. MESNEX tablets are given orally in a dosage equal to 40% of the ifosfamide dose 2 and 6 hours after each dose of ifosfamide. The total daily dose of MESNEX is 100% of the ifosfamide dose. The recommended dosing schedule is outlined in Table 2.

Table 2. Recommended Intravenous and Oral Dosing Schedule
 | 0 Hours | 2 Hours | 6 Hours
Ifosfamide | 1.2 g/m^2 | – | –
MESNEX injection [The dosing schedule should be repeated on each day that ifosfamide is administered. When the dosage of ifosfamide is increased or decreased, the ratio of MESNEX to ifosfamide should be maintained.] | 240 mg/m^2 | – | –
MESNEX tablets | – | 480 mg/m^2 | 480 mg/m^2

The efficacy and safety of this ratio of intravenous and oral MESNEX has not been established as being effective for daily doses of ifosfamide higher than 2 g/m^2.

Patients who vomit within two hours of taking oral MESNEX should repeat the dose or receive intravenous MESNEX.

2.3 Monitoring for Hematuria

Maintain adequate hydration and sufficient urinary output, as required for ifosfamide treatment, and monitor urine for the presence of hematuria. If severe hematuria develops when MESNEX is given according to the recommended dosage schedule, dosage reductions or discontinuation of ifosfamide therapy may be required.

2.4 Preparation for Intravenous Administration and Stability

Preparation

Determine the volume of MESNEX injection for the intended dose.

Dilute the volume of MESNEX injection for the dose in any of the following fluids to obtain a final concentration of 20 mg/mL:

1. 5% Dextrose Injection, USP
2. 5% Dextrose and 0.2% Sodium Chloride Injection, USP
3. 5% Dextrose and 0.33% Sodium Chloride Injection, USP
4. 5% Dextrose and 0.45% Sodium Chloride Injection, USP
5. 0.9% Sodium Chloride Injection, USP
6. Lactated Ringer’s Injection, USP

Stability

The MESNEX injection multidose vials may be stored and used for up to 8 days after initial puncture.

Store diluted solutions at 25°C (77°F). Use diluted solutions within 24 hours.

Do not mix MESNEX injection with epirubicin, cyclophosphamide, cisplatin, carboplatin, and nitrogen mustard.

The benzyl alcohol contained in MESNEX injection vials can reduce the stability of ifosfamide. Ifosfamide and MESNEX may be mixed in the same bag provided the final concentration of ifosfamide does not exceed 50 mg/mL. Higher concentrations of ifosfamide may not be compatible with MESNEX and may reduce the stability of ifosfamide.

Parenteral drug products should be inspected visually for particulate matter and discoloration prior to administration whenever solution and container permit. Any solutions which are discolored, hazy, or contain visible particulate matter should not be used.

3 DOSAGE FORMS AND STRENGTHS

1. MESNEX (mesna) injection: 1 g Multidose Vial, 100 mg/mL
2. MESNEX (mesna) tablets: 400 mg film-coated tablets with functional score

4 CONTRAINDICATIONS

MESNEX is contraindicated in patients known to be hypersensitive to mesna or to any of the excipients [see Warnings and Precautions (5.1)].

5 WARNINGS AND PRECAUTIONS

5.1 Hypersensitivity Reactions

MESNEX may cause systemic hypersensitivity reactions, including anaphylaxis. These reactions may include fever, cardiovascular symptoms (hypotension, tachycardia), acute renal impairment, hypoxia, respiratory distress, urticaria, angioedema, laboratory signs of disseminated intravascular coagulation, hematological abnormalities, increased liver enzymes, nausea, vomiting, arthralgia, and myalgia. These reactions may occur with the first exposure or after several months of exposure. Monitor for signs or symptoms. Discontinue MESNEX and provide supportive care.

5.2 Dermatologic Toxicity

Drug rash with eosinophilia and systemic symptoms and bullous and ulcerative skin and mucosal reactions, consistent with Stevens-Johnson syndrome or toxic epidermal necrolysis have occurred. MESNEX may cause skin and mucosal reactions characterized by urticaria, rash, erythema, pruritus, burning sensation, angioedema, periorbital edema, flushing and stomatitis. These reactions may occur with the first exposure or after several months of exposure. Discontinue MESNEX and provide supportive care.

5.3 Benzyl Alcohol Toxicity

Serious adverse reactions including fatal reactions and the “gasping syndrome” occurred in premature neonates and low-birth weight infants who received benzyl alcohol dosages of 99 to 234 mg/kg/day (blood levels of benzyl alcohol were 0.61 to 1.378 mmol/L). Symptoms associated with “gasping syndrome” and other potential adverse reactions include gradual neurological deterioration, seizures, intracranial hemorrhage, hematological abnormalities, skin breakdown, hepatic and renal failure, hypotension, bradycardia, and cardiovascular collapse. Premature neonates and low-birth weight infants may be more likely to develop these reactions because they may be less able to metabolize benzyl alcohol. The minimum amount of benzyl alcohol at which toxicity may occur is not known. MESNEX injection contains 10.4 mg/mL of the preservative benzyl alcohol. Avoid use of MESNEX injection in premature neonates and low-birth weight infants. MESNEX tablets do not contain benzyl alcohol [see Use in Specific Populations (8.4)].

5.4 Laboratory Test Interferences

False-Positive Urine Tests for Ketone Bodies

A false positive test for urinary ketones may arise in patients treated with MESNEX when using nitroprusside sodium-based urine tests (including dipstick tests). The addition of glacial acetic acid can be used to differentiate between a false positive result (cherry-red color that fades) and a true positive result (red-violet color that intensifies).

False-Negative Tests for Enzymatic CPK Activity

MESNEX may interfere with enzymatic creatinine phosphokinase (CPK) activity tests that use a thiol compound (e.g., N-acetylcysteine) for CPK reactiviation. This may result in a falsely low CPK level.

False-Positive Tests for Ascorbic Acid

MESNEX may cause false-positive reactions in Tillman’s reagent-based urine screening tests for ascorbic acid.

5.5 Use in Patients with a History of Adverse Reactions to Thiol Compounds

MESNEX is a thiol compound, i.e., a sulfhydryl (SH) group-containing organic compound. Hypersensitivity reactions to mesna and to amifostine, another thiol compound, have been reported. It is not clear whether patients who experienced an adverse reaction to a thiol compound are at increased risk for a hypersensitivity reaction to MESNEX.

6 ADVERSE REACTIONS

The following are discussed in more detail in other sections of the labeling.

1. Hypersensitivity Reactions [see Warnings and Precautions (5.1)]
2. Dermatological Toxicity [see Warnings and Precautions (5.2)]
3. Benzyl Alcohol Toxicity [see Warnings and Precautions (5.3)]
4. Laboratory Test Interferences [see Warnings and Precautions (5.4)]
5. Use in Patients with a History of Adverse Reactions to Thiol Compounds [see Warnings and Precautions (5.5)]

6.1 Clinical Trials Experience

Because clinical trials are conducted under widely varying conditions, adverse reaction rates observed in the clinical trials of a drug cannot be directly compared to rates in the clinical trials of another drug and may not reflect the rates observed in practice.

MESNEX adverse reaction data are available from four Phase 1 studies in which single intravenous doses of 600-1200 mg MESNEX injection without concurrent chemotherapy were administered to a total of 53 healthy volunteers and single oral doses of 600-2400 mg of MESNEX tablets were administered to a total of 82 healthy volunteers. The most frequently reported side effects (observed in two or more healthy volunteers) for healthy volunteers receiving single doses of MESNEX injection alone were headache, injection site reactions, flushing, dizziness, nausea, vomiting, somnolence, diarrhea, anorexia, fever, pharyngitis, hyperesthesia, influenza-like symptoms, and coughing. In two Phase 1 multiple-dose studies where healthy volunteers received MESNEX tablets alone or intravenous MESNEX followed by repeated doses of MESNEX tablets, flatulence and rhinitis were reported. In addition, constipation was reported by healthy volunteers who had received repeated doses of intravenous MESNEX.

Additional adverse reactions in healthy volunteers receiving MESNEX alone included injection site reactions, abdominal pain/colic, epigastric pain/burning, mucosal irritation, lightheadedness, back pain, arthralgia, myalgia, conjunctivitis, nasal congestion, rigors, paresthesia, photophobia, fatigue, lymphadenopathy, extremity pain, malaise, chest pain, dysuria, pleuritic pain, dry mouth, dyspnea, and hyperhidrosis. In healthy volunteers, MESNEX was commonly associated with a rapid (within 24 hours) decrease in lymphocyte count, which was generally reversible within one week of administration.

Because MESNEX is used in combination with ifosfamide or ifosfamide-containing chemotherapy regimens, it is difficult to distinguish the adverse reactions which may be due to MESNEX from those caused by the concomitantly administered cytotoxic agents.

Adverse reactions reasonably associated with MESNEX administered intravenously and orally in four controlled studies in which patients received ifosfamide or ifosfamide-containing regimens are presented in Table 3.

Table 3: Adverse Reactions in ≥ 5% of Patients Receiving MESNEX in combination with Ifosfamide-containing Regimens
MESNEX Regimen | Intravenous-Intravenous-Intravenous [Intravenous dosing of ifosfamide and MESNEX followed by either intravenous or oral doses of MESNEX according to the applicable dosage schedule [see Dosage and Administration (2)].] | Intravenous-Oral-Oral
N exposed | 119 (100.0%) | 119 (100%)
Incidence of AEs | 101 (84.9%) | 106 (89.1%)
Nausea | 65 (54.6) | 64 (53.8)
Vomiting | 35 (29.4) | 45 (37.8)
Constipation | 28 (23.5) | 21 (17.6)
Leukopenia | 25 (21.0) | 21 (17.6)
Fatigue | 24 (20.2) | 24 (20.2)
Fever | 24 (20.2) | 18 (15.1)
Anorexia | 21 (17.6) | 19 (16.0)
Thrombocytopenia | 21 (17.6) | 16 (13.4)
Anemia | 20 (16.8) | 21 (17.6)
Granulocytopenia | 16 (13.4) | 15 (12.6)
Asthenia | 15 (12.6) | 21 (17.6)
Abdominal Pain | 14 (11.8) | 18 (15.1)
Alopecia | 12 (10.1) | 13 (10.9)
Dyspnea | 11 (9.2) | 11 (9.2)
Chest Pain | 10 (8.4) | 11 (9.2)
Hypokalemia | 10 (8.4) | 11 (9.2)
Diarrhea | 9 (7.6) | 17 (14.3)
Dizziness | 9 (7.6) | 5 (4.2)
Headache | 9 (7.6) | 13 (10.9)
Pain | 9 (7.6) | 10 (8.4)
Sweating Increased | 9 (7.6) | 2 (1.7)
Back Pain | 8 (6.7) | 6 (5.0)
Hematuria | 8 (6.7) | 7 (5.9)
Injection Site Reaction | 8 (6.7) | 10 (8.4)
Edema | 8 (6.7) | 9 (7.6)
Edema Peripheral | 8 (6.7) | 8 (6.7)
Somnolence | 8 (6.7) | 12 (10.1)
Anxiety | 7 (5.9) | 4 (3.4)
Confusion | 7 (5.9) | 6 (5.0)
Face Edema | 6 (5.0) | 5 (4.2)
Insomnia | 6 (5.0) | 11 (9.2)
Coughing | 5 (4.2) | 10 (8.4)
Dyspepsia | 4 (3.4) | 6 (5.0)
Hypotension | 4 (3.4) | 6 (5.0)
Pallor | 4 (3.4) | 6 (5.0)
Dehydration | 3 (2.5) | 7 (5.9)
Pneumonia | 2 (1.7) | 8 (6.7)
Tachycardia | 1 (0.8) | 7 (5.9)
Flushing | 1 (0.8) | 6 (5.0)

6.2 Postmarketing Experience

The following adverse reactions have been reported in the postmarketing experience of patients receiving MESNEX in combination with ifosfamide or similar drugs, making it difficult to distinguish the adverse reactions which may be due to MESNEX from those caused by the concomitantly administered cytotoxic agents. Because these reactions are reported from a population of unknown size, precise estimates of frequency cannot be made.

Cardiovascular: Hypertension

Gastrointestinal: Dysgeusia

Hepatobiliary: Hepatitis

Nervous System: Convulsion

Respiratory: Hemoptysis

7 DRUG INTERACTIONS

No clinical drug interaction studies have been conducted with MESNEX.

8 USE IN SPECIFIC POPULATIONS

8.1 Pregnancy

Risk Summary

MESNEX is used in combination with ifosfamide or other cytotoxic agents. Ifosfamide can cause fetal harm when administered to a pregnant woman. Refer to the ifosfamide prescribing information for more information on use during pregnancy.

MESNEX injection contains the preservative benzyl alcohol. Because benzyl alcohol is rapidly metabolized by a pregnant woman, benzyl alcohol exposure in the fetus is unlikely [see Warnings and Precautions (5.3) and Use in Specific Populations (8.4)].

The estimated background risk of major birth defects and miscarriage for the indicated populations are unknown. All pregnancies have a background risk of birth defect, loss, or other adverse outcomes. In the U.S. general population, the estimated background risk of major birth defects and miscarriage in clinically recognized pregnancies is 2-4% and 15-20%, respectively.

Data

Animal Data

MESNEX is used in combination with ifosfamide or other cytotoxic agents. Ifosfamide can cause fetal harm including embryo-fetal lethality. Refer to the ifosfamide prescribing information for more information on use during pregnancy.

In embryo-fetal development studies, oral administration of mesna to pregnant rats (500, 1000, 1500, and 2000 mg/kg) and rabbits (500 and 1000 mg/kg) during the period of organogenesis revealed no adverse developmental outcomes at doses approximately 10 times the maximum recommended total daily human equivalent dose based on body surface area.

8.2 Lactation

Risk Summary

MESNEX is used in combination with ifosfamide or other cytotoxic agents. Ifosfamide is excreted in breast milk. Refer to the ifosfamide prescribing information for more information on use during lactation. There are no data on the presence of mesna in human or animal milk, the effect on the breastfed child, or the effect on milk production.

MESNEX injection contains the preservative benzyl alcohol. Because benzyl alcohol is rapidly metabolized by a lactating woman, benzyl alcohol exposure in the breastfed infant is unlikely. However, adverse reactions have occurred in premature neonates and low birth weight infants who received intravenously administered benzyl alcohol-containing drugs [see Warnings and Precautions (5.3) and Use in Specific Populations (8.4)].

Because of the potential for serious adverse reactions in a breastfed child, advise lactating women not to breastfeed during treatment and for 1 week after the last dose of MESNEX or ifosfamide.

8.3 Females and Males of Reproductive Potential

MESNEX is used in combination with ifosfamide or other cytotoxic agents. Ifosfamide can cause fetal harm when administered to a pregnant woman. Refer to the ifosfamide prescribing information for more information on contraception and effects on fertility.

Pregnancy Testing

Verify the pregnancy status of females of reproductive potential prior to initiation of MESNEX in combination with ifosfamide.

Contraception

Females

Advise females of reproductive potential to use effective contraception during treatment with MESNEX in combination with ifosfamide and for 6 months after the last dose.

Males

Advise males with female partners of reproductive potential to use effective contraception during treatment with MESNEX in combination with ifosfamide and for 3 months after the last dose.

8.4 Pediatric Use

MESNEX injection contains the preservative benzyl alcohol which has been associated with serious adverse reactions and death when administered intravenously to premature neonates and low birth weight infants .Avoid use of MESNEX injection in premature neonates and low-birth weight infants [see Warnings and Precautions (5.3)].

8.5 Geriatric Use

Clinical studies of MESNEX did not include sufficient numbers of subjects aged 65 and over to determine whether they respond differently from younger subjects. In general, dose selection for an elderly patient should be cautious, reflecting the greater frequency of decreased hepatic, renal, or cardiac function, and of concomitant disease or other drug therapy. The ratio of ifosfamide to MESNEX should remain unchanged.

8.6 Use in Patients with Renal Impairment

No clinical studies were conducted to evaluate the effect of renal impairment on the pharmacokinetics of MESNEX.

8.7 Use in Patients with Hepatic Impairment

No clinical studies were conducted to evaluate the effect of hepatic impairment on the pharmacokinetics of MESNEX.

10 OVERDOSAGE

There is no known antidote for MESNEX.

In a clinical trial, 11 patients received intravenous MESNEX 10 mg/kg to 66 mg/kg per day for 3 to 5 days. Patients also received ifosfamide or cyclophosphamide. Adverse reactions included nausea, vomiting, diarrhea and fever. An increased rate of these adverse reactions has also been found in oxazaphosphorine-treated patients receiving ≥80 mg MESNEX per kg per day intravenously compared with patients receiving lower doses or hydration treatment only.

Postmarketing, administration of 4.5 g to 6.9 g of MESNEX resulted in hypersensitivity reactions including mild hypotension, shortness of breath, asthma exacerbation, rash, and flushing.

11 DESCRIPTION

MESNEX (mesna) is a detoxifying agent to inhibit the hemorrhagic cystitis induced by ifosfamide. The active ingredient, mesna, is a synthetic sulfhydryl compound designated as sodium-2-mercaptoethane sulfonate with a molecular formula of C2H5NaO3S2and a molecular weight of 164.18. Its structural formula is as follows:

HS–CH2–CH2SO3–Na^+

MESNEX injection is a sterile, nonpyrogenic, aqueous solution of clear and colorless appearance in clear glass multidose vials for intravenous administration. MESNEX injection contains 100 mg/mL mesna, 0.25 mg/mL edetate disodium and sodium hydroxide for pH adjustment. MESNEX injection multidose vials also contain 10.4 mg/mL of benzyl alcohol as a preservative. The solution has a pH range of 7.5-8.5.

MESNEX tablets are white, oblong, scored biconvex film-coated tablets with the imprint M4. They contain 400 mg mesna. The excipients are calcium phosphate, cornstarch, hydroxypropylmethylcellulose, lactose, magnesium stearate, microcrystalline cellulose, polyethylene glycol, povidone, simethicone, and titanium dioxide.

12 CLINICAL PHARMACOLOGY

12.1 Mechanism of Action

Mesna reacts chemically with the urotoxic ifosfamide metabolites, acrolein and 4-hydroxy-ifosfamide, resulting in their detoxification. The first step in the detoxification process is the binding of mesna to 4-hydroxy-ifosfamide forming a non-urotoxic 4-sulfoethylthioifosfamide. Mesna also binds to the double bonds of acrolein and to other urotoxic metabolites and inhibits their effects on the bladder.

12.3 Pharmacokinetics

Absorption

Following oral administration, peak plasma concentrations were reached within 1.5 to 4 hours and 3 to 7 hours for free mesna and total mesna (mesna plus dimesna and mixed disulfides), respectively. Oral bioavailability averaged 58% (range 45 to 71%) for free mesna and 89% (range 74 to 104%) for total mesna based on plasma AUC data from 8 healthy volunteers who received 1200 mg oral or intravenous doses.

Food does not affect the urinary availability of orally administered MESNEX.

Distribution

Mean apparent volume of distribution (Vd) for mesna is 0.652 ± 0.242 L/kg after intravenous administration which suggests distribution to total body water (plasma, extracellular fluid, and intracellular water).

Metabolism

Analogous to the physiological cysteine-cystine system, mesna is rapidly oxidized to its major metabolite, mesna disulfide (dimesna). Plasma concentrations of mesna exceed those of dimesna after oral or intravenous administration.

Excretion

Following intravenous administration of a single 800 mg dose, approximately 32% and 33% of the administered dose was eliminated in the urine in 24 hours as mesna and dimesna, respectively. Mean plasma elimination half-lives of mesna and dimesna are 0.36 hours and 1.17 hours, respectively. Mesna has a plasma clearance of 1.23 L/h/kg.

13 NONCLINICAL TOXICOLOGY

13.1 Carcinogenesis, Mutagenesis, Impairment of Fertility

No long-term studies in animals have been performed to evaluate the carcinogenic potential of mesna.

Mesna was not genotoxic in the in vitroAmes bacterial mutagenicity assay, the in vitromammalian lymphocyte chromosomal aberration assay or the in vivomouse micronucleus assay.

No studies on male or female fertility were conducted. No signs of male or female reproductive organ toxicity were seen in 6-month oral rat studies (≤ 2000 mg/kg/day) or 29-week oral dog studies (520 mg/kg/day) at doses approximately 10-fold higher than the maximum recommended human dose on a body surface area basis.

14 CLINICAL STUDIES

14.1 Intravenous MESNEX

Hemorrhagic cystitis produced by ifosfamide is dose dependent (Table 4). At a dose of 1.2 g/m^2ifosfamide administered daily for 5 days, 16 to 26% of the patients who received conventional uroprophylaxis (high fluid intake, alkalinization of the urine, and the administration of diuretics) developed hematuria (>50 RBC per hpf or macrohematuria) (Studies 1, 2, and 3). In contrast, none of the patients who received mesna injection together with this dose of ifosfamide developed hematuria (Studies 3 and 4). In two randomized studies, (Studies 5 and 6), higher doses of ifosfamide, from 2 g/m^2to 4 g/m^2administered for 3 to 5 days, produced hematuria in 31 to 100% of the patients. When MESNEX was administered together with these doses of ifosfamide, the incidence of hematuria was less than 7%.

Table 4. Percent of MESNEX Patients Developing Hematuria (≥50 RBC/hpf or macrohematuria)
Study | Conventional Uroprophylaxis (number of patients) | Standard MESNEX Intravenous Regimen (number of patients)
Uncontrolled Studies [Ifosfamide dose 1.2 g/m 2 d x 5]
Study 1 | 16% (7/44) | -
Study 2 | 26% (11/43) | -
Study 3 | 18% (7/38) | 0% (0/21)
Study 4 | - | 0% (0/32)
Controlled Studies [Ifosfamide dose 2 g/m 2 to 4 g/m 2 d x 3 to 5]
Study 5 | 31% (14/46) | 6% (3/46)
Study 6 | 100% (7/7) | 0% (0/8)

14.2 Oral MESNEX

Clinical studies comparing recommended intravenous and oral MESNEX dosing regimens demonstrated incidences of grade 3 to 4 hematuria of <5%. Study 7 was an open label, randomized, two-way crossover study comparing three intravenous doses with an initial intravenous dose followed by two oral doses of MESNEX in patients with cancer treated with ifosfamide at a dose of 1.2 g/m^2to 2.0 g/m^2for 3 to 5 days. Study 8 was a randomized, multicenter study in cancer patients receiving ifosfamide at 2.0 g/m^2for 5 days. In both studies, development of grade 3 or 4 hematuria was the primary efficacy endpoint. The percent of patients developing hematuria in each of these studies is presented in Table 5.

Table 5. Percent of MESNEX Patients Developing Grade 3 or 4 Hematuria
 | MESNEX Dosing Regimen
Study | Standard Intravenous Regimen; (number of patients) | Intravenous + Oral Regimen; (number of patients)
Study 7 | 0% (0/30) | 3.6% (1/28)
Study 8 | 3.7% (1/27) | 4.3% (1/23)

16 HOW SUPPLIED/STORAGE AND HANDLING

MESNEX (mesna) injection 100 mg/mL

1. NDC 0338-1305-01 1 g Multidose Vial, Box of 1 vial of 10 mL
2. NDC 0338-1305-03 1 g Multidose Vial, Box of 10 vials of 10 mL
3. Store at 20°C to 25°C (68°F to 77°F), excursions permitted to 15°C to 30°C (59°F to 86°F) [see USP Controlled Room Temperature]

If MESNEX is co-administered with ifosfamide, refer to the ifosfamide prescribing information for safe handling instructions.

MESNEX (mesna) tablets

1. NDC 67108-3565-9 400 mg scored tablets packaged in box of 10 tablets
2. Store at 20°C to 25°C (68°F to 77°F), excursions permitted to 15°C to 30°C (59°F to 86°F) [see USP Controlled Room Temperature]

17 PATIENT COUNSELING INFORMATION

See FDA-approved patient labeling (Patient Information).

Hypersensitivity

1. Advise the patient to discontinue MESNEX and seek immediate medical attention if any signs or symptoms of a hypersensitivity reaction, including systemic anaphylactic reactions occur [see Warnings and Precautions (5.1)].

Dosing Instructions

1. Advise the patient to take MESNEX at the exact time and in the exact amount as prescribed. Advise the patient to contact their healthcare provider if they vomit within 2 hours of taking oral MESNEX, or if they miss a dose of oral MESNEX [see Dosage and Administration (2.2)].

Hemorrhagic Cystitis

1. MESNEX does not prevent hemorrhagic cystitis in all patients nor does it prevent or alleviate any of the other adverse reactions or toxicities associated with ifosfamide. Advise the patient to report to their healthcare provider if his/her urine has turned a pink or red color [see Dosage and Administration (2.3)].
2. Advise the patient to drink 1 to 2 liters of fluid each day during MESNEX therapy [see Dosage and Administration (2.3)].

Dermatologic Toxicity

1. Advise the patient that Stevens-Johnson syndrome, toxic epidermal necrolysis, and drug rash with eosinophilia and systemic symptoms and bullous and ulcerative skin and mucosal reactions have occurred with MESNEX. Advise the patient to report to their healthcare provider if signs and symptoms of these syndromes occur [see Warnings and Precautions (5.2)].

Benzyl Alcohol Toxicity

1. Advise patients that serious adverse reactions are associated with the benzyl alcohol found in MESNEX and other medications in premature neonates and low-birth weight infants [see Warnings and Precautions (5.3)and Use in Specific Populations (8.4)].

Embryo-Fetal Toxicity

1. MESNEX is used in combination with ifosfamide. Ifosfamide or other cytotoxic agents can cause fetal harm when administered to a pregnant woman. Inform female patients of the risk to a fetus and potential loss of the pregnancy. Advise females to inform their healthcare provider if they are pregnant or become pregnant [see Use in Specific Populations (8.1)].

Contraception

1. Advise females of reproductive potential to use effective contraception during treatment with MESNEX in combination with ifosamide and for 6 months after the last dose [see Use in Specific Populations (8.3)].
2. Advise male patients with female partners of reproductive potential to use effective contraception during treatment with MESNEX in combination with ifosamide and for 3 months after the last dose [see Use in Specific Populations (8.3)].

Lactation

1. Advise lactating women not to breastfeed during treatment with MESNEX or ifosfamide and for 1 week after the last dose [see Use in Specific Populations (8.2)].

BaxterLogo
MESNEX (mesna) injection manufactured by:

MESNEX (mesna) tablets manufactured for:

1. Baxter Healthcare Corporation
  Deerfield, IL 60015 USA
  For Product Inquiry 1800 ANA DRUG (1-800-262-3784)

Made in Germany

Baxter and Mesnex are registered trademarks of Baxter International Inc.

Material No. HA-30-01-814

Patient Information
MESNEX (MES-nex)
(mesna)
tablets

MESNEX (MES-nex)
(mesna)
injection

What is the most important information I should know about MESNEX?

MESNEX can cause serious allergic reactions and skin reactions.These serious reactions can happen the first time you are treated with MESNEX or after several months of treatment with MESNEX. Stop treatment with MESNEX and go to the nearest hospital emergency room right away if you develop any of the symptoms listed below:

- fever
- swelling of your face, lips, mouth, or tongue
- trouble breathing or wheezing
- itching
- burning
- skin rash or hives
- skin redness or swelling

- skin blisters or peeling
- feel lightheaded or faint
- feel like your heart is racing
- nausea
- vomiting
- joint or muscle aches
- mouth sores

1. See “ What are the possible side effects of MESNEX?” for more information about side effects.

What is MESNEX?

MESNEX is a prescription medicine used to reduce the risk of inflammation and bleeding of the bladder (hemorrhagic cystitis) in people who receive ifosfamide (a medicine used to treat cancer).

MESNEX is not for use to reduce the risk of blood in the urine (hematuria) due to other medical conditions.

Do not take MESNEX tablets or receive MESNEX by intravenous (IV) infusion ifyou are allergic to mesna or any of the ingredients in MESNEX. See the end of this leaflet for a complete list of ingredients in MESNEX.

Before you take or receive MESNEX, tell your healthcare provider about all of your medical conditions, including if you:

- are allergic to any medicines
- are pregnant or plan to become pregnant.
- Females who are able to become pregnant:
- Your healthcare provider will verify if you are pregnant or not before you start treatment with MESNEX and ifosfamide.
  - You should use effective birth control (contraception) during treatment with MESNEX and ifosfamide and for 6 months after the last dose.
  - Tell your healthcare provider if you become pregnant during treatment with MESNEX and ifosfamide.
- Maleswith female partners who are able to become pregnant should use effective birth control during treatment with MESNEX and ifosfamide and for 3 months after the last dose.
- You should also read the ifosfamide Prescribing Information for important pregnancy, contraception, and infertility information.
- are breastfeeding or plan to breastfeed. It is not known if MESNEX passes into your breast milk. Do not breastfeed during treatment and for 1 week after the last dose of MESNEX or ifosfamide.

Tell your healthcare provider about all the medicines you take,including prescription and over-the-counter medicines, vitamins, and herbal supplements.

How will I receive MESNEX?

- MESNEX is given on the same day that you receive ifosfamide.
- MESNEX can be given by an intravenous (IV) infusion into a vein or tablets taken by mouth.
- You will receive MESNEX in one of two ways:
- MESNEX intravenous (IV) infusion into a vein at the time you receive ifosfamide and 4 and 8 hours after you receive ifosfamide, OR
- MESNEX intravenous (IV) infusion into a vein at the time you receive ifosfamide and MESNEX tablets taken by mouth 2 and 6 hours after you receive ifosfamide.
- Take MESNEX tablets at the exact times and the exact dose your healthcare provider tells you to take it.
- During treatment with MESNEX intravenous (IV) infusion or MESNEX tablets, you should drink 4 to 8 cups of liquid (1 to 2 liters) each day.
- Tell your healthcare provider if you:
- vomit within 2 hours of taking MESNEX tablets by mouth
- miss a dose of MESNEX tablets
- have pink or red colored urine

What are the possible side effects of MESNEX?

MESNEX may cause serious side effects, including:

See “What is the most important information I should know about MESNEX?”

- MESNEX that is given by intravenous (IV) infusion contains the preservative benzyl alcohol.Benzyl alcohol has been shown to cause serious side effects and death in premature newborns and low-birth weight babies. Avoid use of MESNEX injection in premature newborns and low birth weight infants. MESNEX tablets do not contain benzyl alcohol.

The most common side effects of MESNEX when given with ifosfamide include:

- nausea
- vomiting
- constipation
- decreased white blood cell count
- tiredness
- fever
- decreased appetite
- decreased platelet count

- decreased red blood cell count
- diarrhea
- weakness
- stomach (abdomen) pain
- headache
- hair loss
- sleepiness

These are not all the possible side effects of MESNEX.

Call your doctor for medical advice about side effects. You may report side effects to FDA at 1-800-FDA-1088.

How should I store MESNEX tablets?

- Store MESNEX tablets at room temperature between 68°F to 77°F (20°C to 25°C).

Keep MESNEX and all medicines out of the reach of children.

General information about the safe and effective use of MESNEX.

Medicines are sometimes prescribed for purposes other than those listed in a Patient Information leaflet. Do not use MESNEX for a condition for which it was not prescribed. Do not give MESNEX to other people, even if they have the same symptoms that you have. It may harm them. You can ask your pharmacist or healthcare provider for information about MESNEX that is written for health professionals.

What are the ingredients in MESNEX?

Active ingredient:mesna

Inactive ingredients:

MESNEX injection:edetate disodium, sodium hydroxide, and benzyl alcohol as a preservative.

MESNEX tablets:calcium phosphate, cornstarch, hydroxypropylmethylcellulose, lactose, magnesium stearate, microcrystalline cellulose, polyethylene glycol, povidone, simethicone, and titanium dioxide.

Manufactured by: Baxter Healthcare Corporation, Deerfield, IL 60015 USA
Made in Germany
Baxter and Mesnex are registered trademarks of Baxter International Inc.
For more information, call 1-800-262-3784.

This Patient Information has been approved by the U.S. Food and Drug Administration. Revised: 12 2018

PACKAGE LABEL - PRINCIPAL DISPLAY PANEL

1g Multidose Vial

1 Multidose Vial NDC 0338-1305-01

Mesnex
(mesna) Injection

FOR INTRAVENOUS USE

1g/vial Rx only

N (01) 1 03 0338 1305 01 4

Lot Number / Expires:

JMXXXA

JJJJ - MM

Each vial contains 1 gram of
mesna in 10 mL water.
1% benzyl alcohol is added as a
preservative.
See insert for dosing information.
Store at 20° - 25°C (68° - 77°F),
excursions permitted to
15° - 30°C (59° - 86°F)[see USP
Controlled Room Temperature]

Manufactured by:
Baxter Healthcare Corporation
Deerfield, IL 60015 USA

USAHA-65-01-568 C 93

1 Multidose Vial
NDC 0338-1305-01

MESNEX
(mesna) Injection

1g/vial

FOR INTRAVENOUS USE

Rx only

BaxterLogo
Manufactured by
Baxter Healthcare Corporation
Deerfield, IL 60015 USA

(01) 00303381305017
(21) XXXXXXXXXXXX
(17) JJMMTT
(10) JMXXXA

Barcode

MESNEX
mesna Injection

1g/vial

Barcode

HA-80-02-158
USA

Fragile:
Handle with care.
Store at 20° - 25°C
(68°-77°F) excursions
permitted to 15° - 30°C
(59° - 86°F) [see USP
Controlled Room Temperature].

BaxterLogo
Manufactured by
Baxter Healthcare Corporation
Deerfield, IL 60015 USA

C
203

1 Multidose Vial
NDC 0338-1305-01

MESNEX
(mesna) Injection

1g/vial

FOR INTRAVENOUS USE

Rx only

BaxterLogo
Manufactured by
Baxter Healthcare Corporation
Deerfield, IL 60015 USA

Lot/Exp:
JMXXXA
JJJJ - MM

2639B3994

Barcode

Folding Box Logo
Can Be Recycled

Each vial contains 1 g mesna in
10 mL water, Mesnex is a sterile
and nonpyrogenic solution
containing 10%
sodium-2-mercaptoehane
sulfonate (mesna) in water for
injection with 0.025% edetate
disodium and sodium hydroxide
to adjust pH to 7.5 to 8.5.
1% benzyl alcohol is added as
a preservative.

Dosage: See package insert for
directions for use. Should not
be prescribed without thorough
knowledge of dose, indications
and toxicology as contained in
accompanying literature.

Manufactured by:
Baxter Healthcare Corporation
Deerfield, IL 60015 USA

Made in Germany

Schwarz

P 186 C

10 Multidose Vials NDC 0338-1305-03

1g

MESNEX

(mesna) Injection

BaxterLogo
Manufactured by
Baxter Healthcare Corporation
Deerfield, IL 60015 USA

10 Multidose Vials NDC 0338-1305-03

1g

N3 0338130503 1

MESNEX
(mesna) Injection

Each vial contains 1 g mesna in 10mL water. Mesnex is a sterile and nonpyrogenic solution
containing 10% sodium-2-mercaptoehane sulfonate (mesna) in water for injection with 0.025%
edetate disodium and sodium hydroxide to adjust pH to 7.5 to 8.5. 1% benzyl alcohol is added as
a preservative.

Fragile:Handle with care. Store at 20° - 25°C (68°-77°F) see excursions permitted to 15° - 30°C
(59° - 86°F) [see USP Controlled Room Temperature] U.S. Patent No 5,696, 172

FOR INTRAVENOUS USE

Dosage:See package insert for directions for use. Should not be prescribed without thorough
knowledge of dose, indications and toxicology as contained in accompanying literature.

Manufactured by:
Baxter Healthcare Corporation
Deerfield, IL 60015 USA

Made in Germany

Rx only

HA-80-01-627
USA

10 Multidose Vials NDC 0338-1305-03

1g

MESNEX
(mesna) Injection

FOR INTRAVENOUS USE
10 Multidose Vials

C
53

10 Multidose Vials NDC 0338-1305-03

1g

2639B3913

Lot:
Exp.:

MESNEX
(mesna) Injection

Each vial contains 1 g mesna in 10mL water. Mesnex is a sterile and nonpyrogenic solution
containing 10% sodium-2-mercaptoehane sulfonate (mesna) in water for injection with 0.025%
edetate disodium and sodium hydroxide to adjust pH to 7.5 to 8.5. 1% benzyl alcohol is added as
a preservative.

Fragile:Handle with care. Store at 20° - 25°C (68°-77°F) see excursions permitted to 15° - 30°C
(59° - 86°F) [see USP Controlled Room Temperature] U.S. Patent No 5,696, 172

FOR INTRAVENOUS USE

Dosage:See package insert for directions for use. Should not be prescribed without thorough
knowledge of dose, indications and toxicology as contained in accompanying literature.

Manufactured by:
Baxter Healthcare Corporation
Deerfield, IL 60015 USA

Made in Germany

Rx only

Folding Box
Logo
Can Be Recycled

10 Multidose Vials NDC 0338-1305-03

1g

MESNEX
(mesna) Injection

FOR INTRAVENOUS USE
10 Multidose Vials